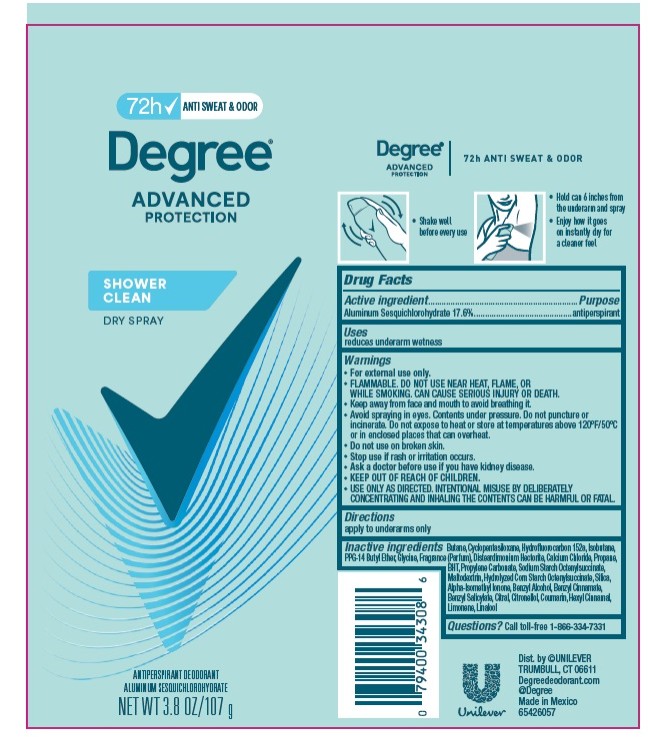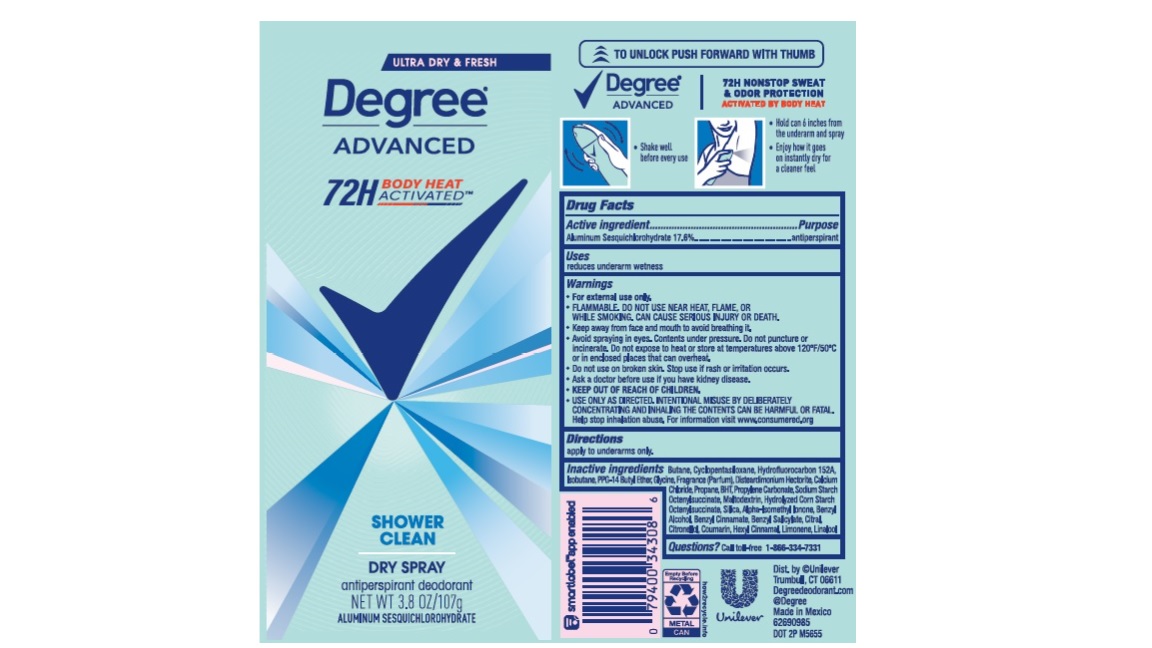 DRUG LABEL: Degree
NDC: 64942-2181 | Form: AEROSOL, SPRAY
Manufacturer: Conopco, Inc. d/b/a Unilever
Category: otc | Type: HUMAN OTC DRUG LABEL
Date: 20260210

ACTIVE INGREDIENTS: ALUMINUM SESQUICHLOROHYDRATE 17.6 g/100 g
INACTIVE INGREDIENTS: PROPYLENE CARBONATE; MALTODEXTRIN; SILICON DIOXIDE; GLYCINE; BENZYL SALICYLATE; COUMARIN; LIMONENE, (+)-; BENZYL CINNAMATE; ISOBUTANE; .BETA.-CITRONELLOL, (R)-; BUTANE; 1,1-DIFLUOROETHANE; CYCLOMETHICONE 5; PPG-14 BUTYL ETHER; DISTEARDIMONIUM HECTORITE; CALCIUM CHLORIDE; CITRAL; ISOMETHYL-.ALPHA.-IONONE; BENZYL ALCOHOL; .ALPHA.-HEXYLCINNAMALDEHYDE; LINALOOL, (+/-)-; PROPANE; BUTYLATED HYDROXYTOLUENE

Degree Advanced Shower Clean Dry Spray 72H Antiperspirant Deodorant

Drug Facts

Active ingredient

Aluminum Sesquichlorohydrate (17.6%)

Purpose

antiperspirant

Uses

reduces underarm wetness

Directions

For underarms use only

Inactive ingredients

Butane, Cyclopentasiloxane, Hydrofluorocarbon 152a, Isobutane, PPG-14 Butyl Ether, Glycine, Fragrance (Parfum), Disteardimonium Hectorite, Calcium Chloride, Propane, BHT, Propylene Carbonate, Sodium Starch Octenylsuccinate, Maltodextrin, Hydrolyzed Corn Starch Octenylsuccinate, Silica, Alpha-Isomethyl Ionone, Benzyl Alcohol, Benzyl Cinnamate, Benzyl Salicylate, Citral, Citronellol, Coumarin, Geraniol, Hexyl Cinnamal, Limonene, Linalool

Questions?

Call toll-free 1-866-334-7331